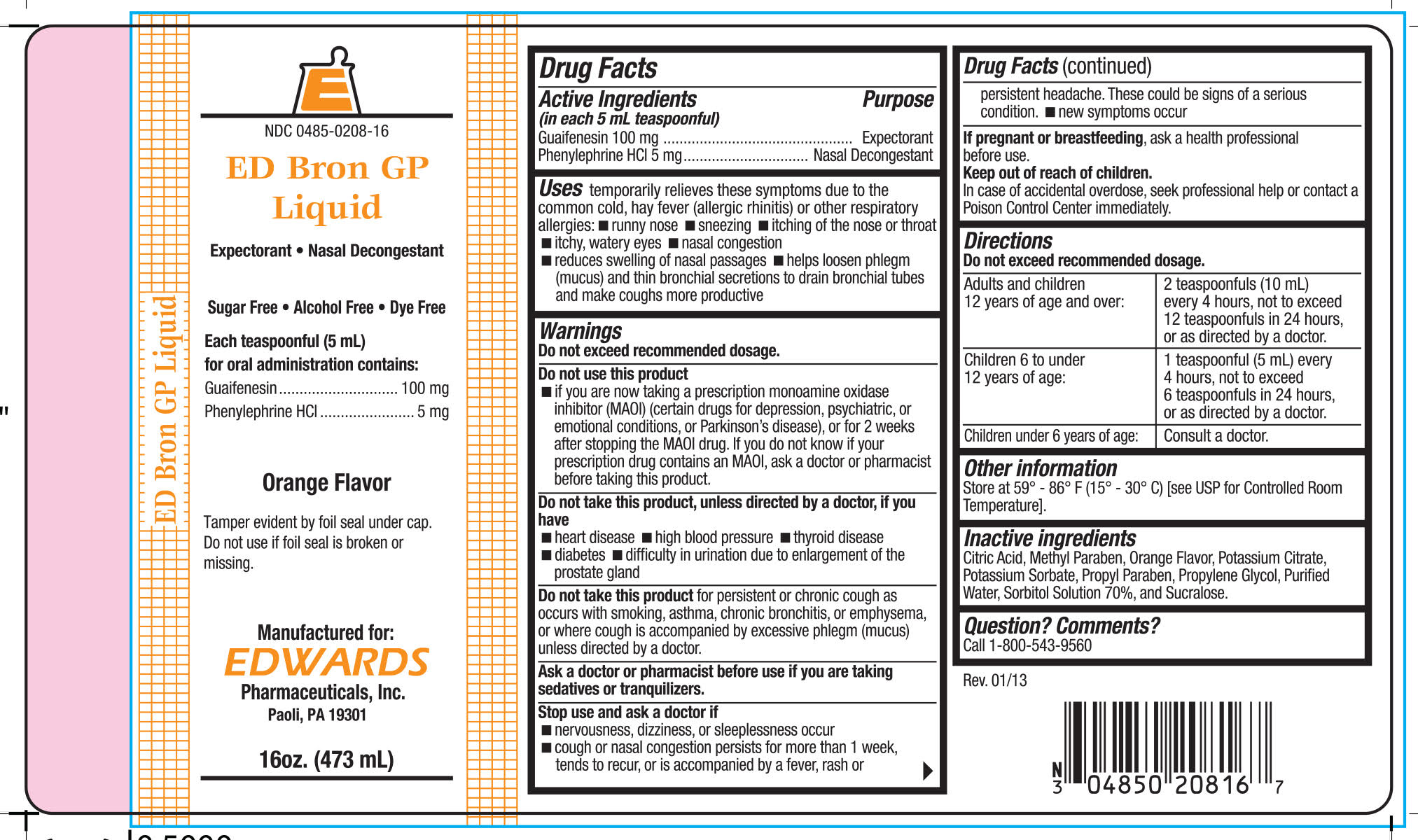 DRUG LABEL: ED BRON GP
NDC: 0485-0208 | Form: LIQUID
Manufacturer: EDWARDS PHARMACEUTICALS, INC.
Category: otc | Type: HUMAN OTC DRUG LABEL
Date: 20251028

ACTIVE INGREDIENTS: GUAIFENESIN 100 mg/5 mL; PHENYLEPHRINE HYDROCHLORIDE 5 mg/5 mL
INACTIVE INGREDIENTS: CITRIC ACID MONOHYDRATE; METHYLPARABEN; POTASSIUM CITRATE; POTASSIUM SORBATE; PROPYLPARABEN; PROPYLENE GLYCOL; WATER; SORBITOL; SUCRALOSE

ED BRON GP

Drug Facts

ACTIVE INGREDIENT

Active Ingredients (in each 5 mL teaspoonful) | Purpose
Guaifenesin 100 mg | Expectorant
Phenylephrine HCl 5 mg | Nasal Decongestant

Uses

temporarily relieves these symptoms due to the common cold, hay fever (allergic rhinitis) or other respiratory allergies:

- runny nose
- sneezing
- itching of the nose or throat
- itchy, watery eyes
- nasal congestion
- reduces swelling of nasal passages
- helps loosen phlegm (mucus) and thin bronchial secretions to drain bronchial tubes and make coughs more productive

Warnings

Do not exceed recommended dosage.

Do not use this product

- if you are now taking a prescription monoamine oxidase inhibitor (MAOI) (certain drugs for depression, psychiatric, or emotional conditions, or Parkinson's disease), or for 2 weeks after stopping the MAOI drug. If you do not know if your prescription drug contains an MAOI, ask a doctor or pharmacist before taking this product.

Do not take this product, unless directed by a doctor, if you have

- heart disease
- high blood pressure
- thyroid disease
- diabetes
- difficulty in urination due to enlargement of the prostate gland

DO NOT USE

Do not take this product for persistent or chronic cough as occurs with smoking, asthma, chronic bronchitis, or emphysema, or where cough is accompanied by excessive phlegm (mucus) unless directed by a doctor.

Ask a doctor or pharmacist before use if you are taking sedatives or tranquilizers.

Stop use and ask a doctor if

- nervousness, dizziness, or sleeplessness occur
- cough or nasal congestion persists for more than 1 week, tends to recur, or is accompanied by a fever, rash or persistent headache. These could be signs of a serious condition.
- new symptoms occur

PREGNANCY OR BREAST FEEDING

If pregnant or breastfeeding, ask a health professional before use.

Keep out of reach of children.

In case of accidental overdose, seek professional help or contact a Poison Control Center immediately.

Directions

Do not exceed recommended dosage.

Adults and children 12 years of age and over: | 2 teaspoonfuls (10 mL) every 4 hours, not to exceed 12 teaspoonfuls in 24 hours, or as directed by a doctor.
Children 6 to under 12 years of age: | 1 teaspoonful (5 mL) every 4 hours, not to exceed 6 teaspoonfuls in 24 hours, or as directed by a doctor.
Children under 6 years of age: | Consult a doctor.

Other information

Store at 59° - 86° F (15° - 30° C) [see USP for Controlled Room Temperature].

Inactive ingredients

Citric Acid, Methyl Paraben, Orange Flavor, Potassium Citrate, Potassium Sorbate, Propyl Paraben, Propylene Glycol, Purified Water, Sorbitol Solution 70%, and Sucralose.

Question? Comments?

Call 1-800-543-9560

PRINCIPAL DISPLAY PANEL - 473 mL Bottle Label

NDC 0485-0208-16

ED Bron GP Liquid

Expectorant • Nasal Decongestant

Sugar Free • Alcohol Free • Dye Free

Each teaspoonful (5 mL)
for oral administration contains:
Guaifenesin 100 mg
Phenylephrine HCl 5 mg

Orange Flavor

Tamper evident by foil seal under cap.
Do not use if foil seal is broken or missing.

Manufactured for:
EDWARDS Pharmaceuticals, Inc.
Paoli, PA 19301

16oz. (473 mL)